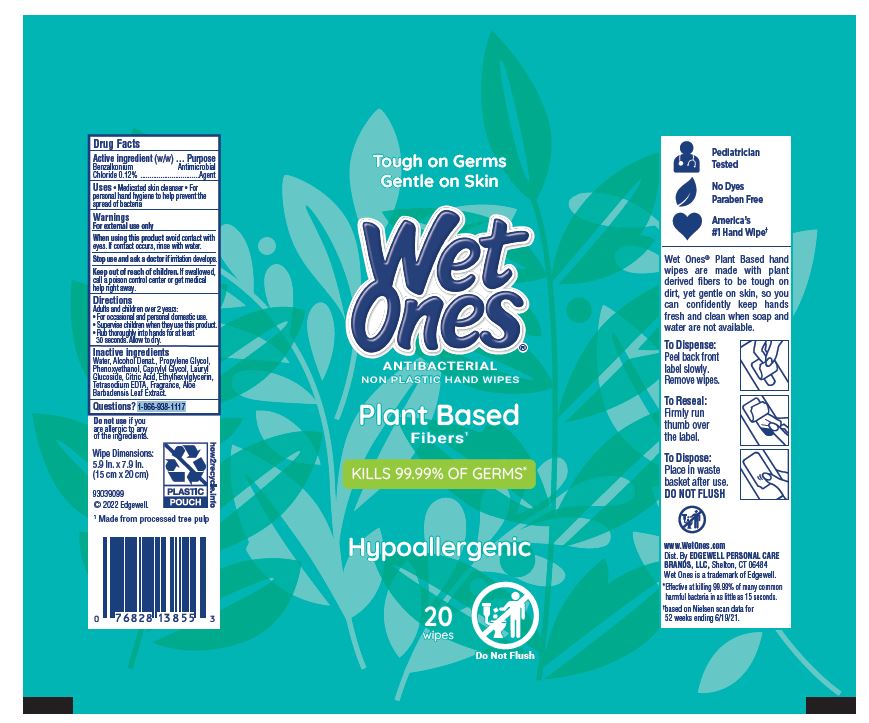 DRUG LABEL: Wet Ones Antibacterial Non Plastic Hand Wipes
NDC: 63354-909 | Form: SWAB
Manufacturer: Edgewell Personal Care Brands LLC
Category: otc | Type: HUMAN OTC DRUG LABEL
Date: 20241001

ACTIVE INGREDIENTS: BENZALKONIUM CHLORIDE 0.12 g/100 g
INACTIVE INGREDIENTS: CITRIC ACID MONOHYDRATE; ETHYLHEXYLGLYCERIN; PHENOXYETHANOL; ALOE VERA LEAF; DEHYDRATED ALCOHOL; WATER; PROPYLENE GLYCOL; LAURYL GLUCOSIDE

Active ingredient

Benzalkonium Chloride 0.12%

Purpose

Antimicrobial Agent

Uses

Medicated skin cleanser • For personal hand hygiene to help prevent the spread of bacteria

Warnings

For external use only

When using this product

avoid contact with eyes. If contact occurs, rinse with water

Stop use and ask a doctor

if irritation develops.

Keep out of reach of children

If swallowed, call a poison control center or get medical help right away.

Directions

- For occasional and personal domestic use.
- Supervise children when they use this product.
- Rub thoroughly into hands for at least 30 seconds. Allow to dry.

Inactive ingredients

Water, Alcohol Denat., Propylene Glycol,
Phenoxyethanol, Caprylyl Glycol, Lauryl
Glucoside, Citric Acid, Ethylhexylglycerin,
Tetrasodium EDTA, Fragrance, Aloe
Barbadensis Leaf Extract.

Questions?

1-866-938-1117

PRINCIPAL DISPLAY PANEL

Tough on Germs

Gentle on Skin

Wet

Ones

ANTIBACTERIAL

NON PLASTIC HAND WIPES

Plant Based

Fibers

KILLS 99.99% OF GERMS

Hypoallergenic

20

wipes

Do Not Flush